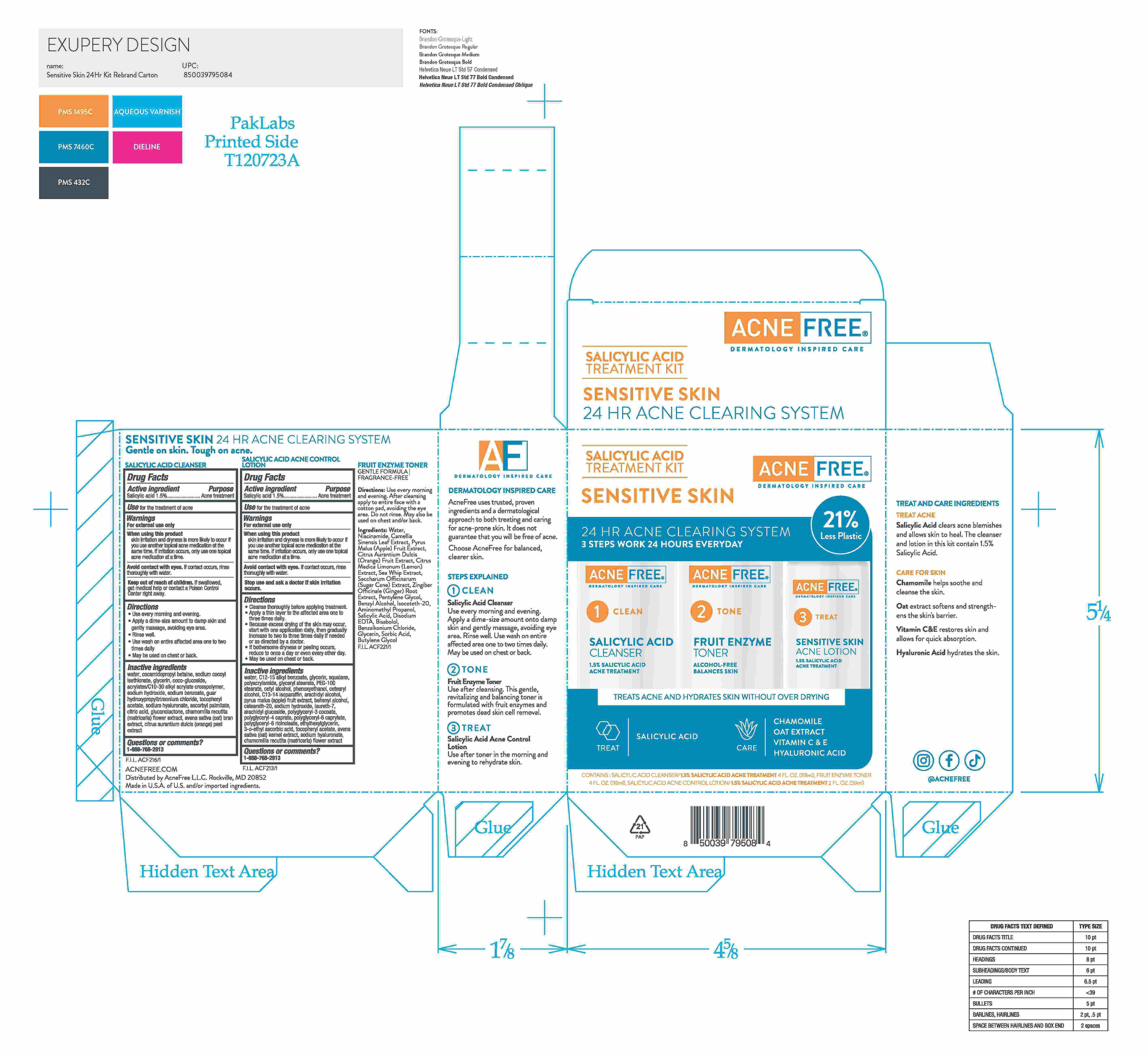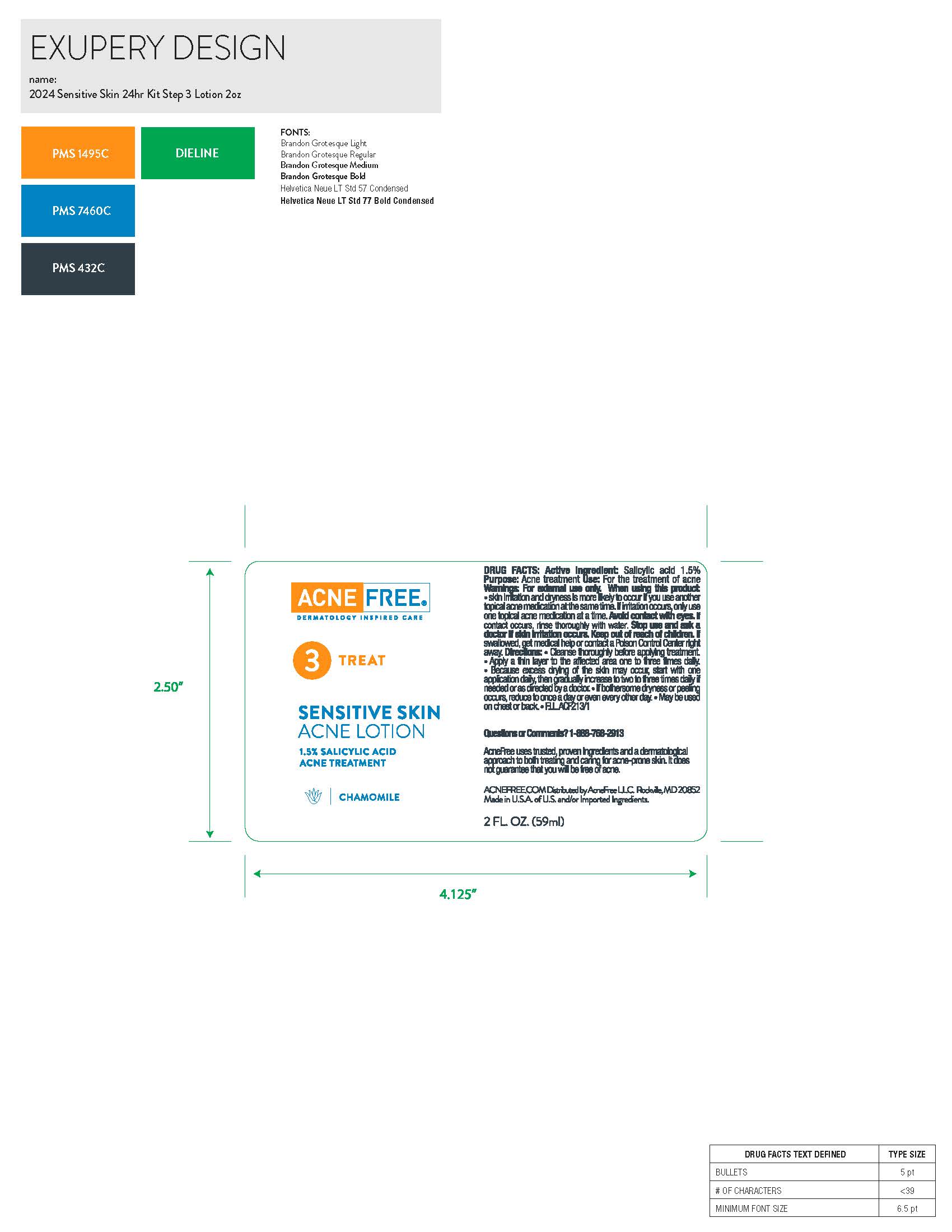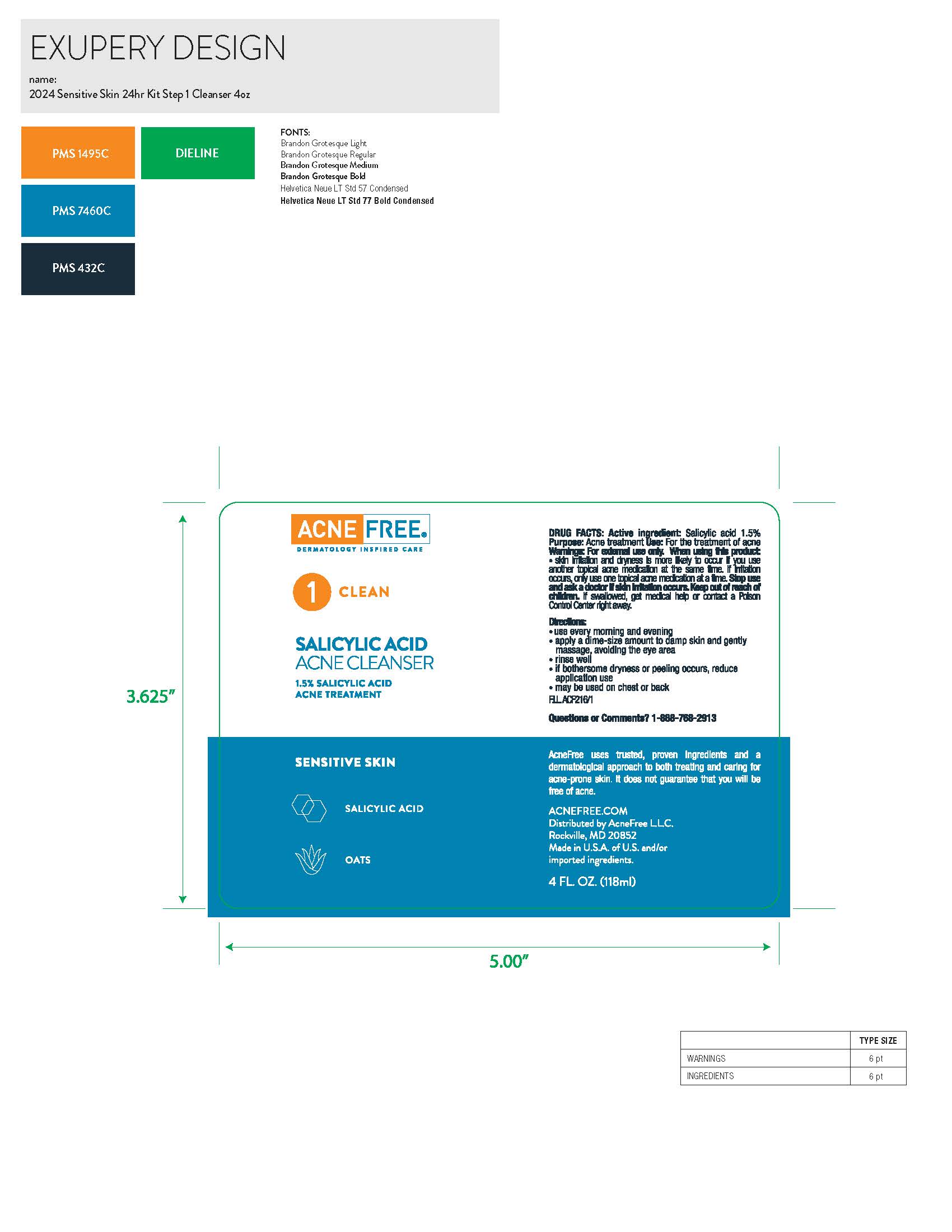 DRUG LABEL: 24 Hour Sensitive Skin Acne Clearing System
NDC: 80861-118 | Form: KIT | Route: TOPICAL
Manufacturer: Acne Free LLC
Category: otc | Type: HUMAN OTC DRUG LABEL
Date: 20250714

ACTIVE INGREDIENTS: SALICYLIC ACID 15 mg/1 mL; SALICYLIC ACID 15 mg/1 mL
INACTIVE INGREDIENTS: GLYCERYL STEARATE SE; POLYGLYCERYL-6 CAPRYLATE; PHENOXYETHANOL; POLYACRYLAMIDE (10000 MW); CETYL ALCOHOL; C13-14 ISOPARAFFIN; PYRUS MALUS (APPLE) FRUIT; C12-15 ALKYL BENZOATE; LAURETH-7; ARACHIDYL GLUCOSIDE; .ALPHA.-TOCOPHEROL ACETATE, D-; BEHENYL ALCOHOL; AVENA SATIVA (OAT) KERNEL OIL; WATER; SQUALANE; GLYCERIN; CETEARYL ALCOHOL; CETEARETH-20; POLYGLYCERYL-3 STEARATE; POLYGLYCERYL-4 CAPRATE; POLYGLYCERYL-6 RICINOLEATE; 3-O-ETHYL ASCORBIC ACID; MATRICARIA CHAMOMILLA FLOWERING TOP OIL; ETHYLHEXYLGLYCERIN; PEG-100 STEARATE; ARACHIDYL ALCOHOL; SODIUM HYDROXIDE; SODIUM HYALURONATE; COCO-GLUCOSIDE; ACRYLATES/C10-30 ALKYL ACRYLATE CROSSPOLYMER (60000 MPA.S); CITRIC ACID; AVENA SATIVA (OAT) BRAN; SODIUM HYDROXIDE; SODIUM BENZOATE; WATER; GLYCERIN; GUAR HYDROXYPROPYLTRIMONIUM CHLORIDE; .ALPHA.-TOCOPHEROL ACETATE; CITRUS AURANTIUM DULCIS (ORANGE) PEEL OIL; SODIUM COCOYL ISETHIONATE; GLUCONOLACTONE; MATRICARIA CHAMOMILLA FLOWERING TOP OIL; COCAMIDOPROPYL BETAINE; SODIUM HYALURONATE; ASCORBYL PALMITATE

Active Ingredient

Salicylic acid 1.5%

Purpose

Acne treatment

Use

for treatment of acne

Warnings

For external use only

When using this product Avoid contact with eyes

skin irritation and dryness is more likely to occur if you use another topical acne medication at the same time. If irritation occurs, only use one topical acne medication at a time.

If contact occurs, rinse thoroughly with water

Keep out of reach of children

If swallowed, get medical help or contact a Poison Control Center right away

When using this product

skin initation and dryness is more likely to occur r
you use another topical acne medic,rnon at the same time. If irritation occurs, only use one topical
acne medication at a time.

Directions

- Use every morning and evening
- Apply a dime-size amount to damp skin and gently massage, avoiding eye area
- Rinse well
- Use wash on entire affected area one to two times daily
- May be used on chest or back

Inactive ingredients

water, cocamidopropyl betaine, sodiumcocoyl
isethionate, glycerin, coco-glucoside, acrylates/Cl 0-30 alkyl acrylate crosspolymer, sodium
hydroxide, sodium benzoate, guar hydroxypropyltrimonium chloride, tocopheryl acetate, sodium
hyaluronate, ascorbyl palmitate, citric acid, gluconolactone, chamomilla recutita (matricaria)
flower extract, avena sativa (oat) bran extract, citrus aurantium dulcis (orange) peel extract

Questions or comments?

1-888-768-2913

Active ingredient

Salicylic acid 1.5%

Purpose

Acne treatment

Use

for the treatment of acne

Warnings

For external use only

1. When using this product 2. Avoid contact with eyes

1. skin initation and dryness is more likely to occur r
you use another topical acne medic,rnon at the same time. If irritation occurs, only use one topical
acne medication at a time.

2. If contact occurs, rinse thoroughly with water

Directions

• Cleanse thoroughly before applying treatment.
• Apply a thin layer to the affected area one to three times daily.
• Because excess drying of the skin may occur, start with one application daily, then gradually
increase to two to three times daily if needed or as directed by a doctor.
• If bothersome dryness or peeling occurs, reduce to once a day or even every other day.
• May be used on chest or back.

Inactive ingredients

water, Cl2-15 alkyl benzoate, glycerin, squalane,
polyacrylamide, glyceryl stearate, PEG-100 stearate, cetyl alcohol, phenoxyethanol, cetearyl
alcohol, Cl3-14 isoparaffin, arachidyl alcohol, pyrus malus (apple) fruit extract, behenyl alcohol,
ceteareth-20, sodium hydroxide, laureth-7, arachidyl glucoside, polyglyceryl-3 cocoate,
polyglyceryl-4 caprate, polyglyceryl-6 caprylate, polyglyceryl-6 ricinoleate, ethylhexylglycerin,
3-o-ethyl ascorbic acid, tocopheryl acetate, avena saliva (oat) kernel extract, sodium hyaluronate,
chamomilla recutita (matricaria) flower extract

Questions or comments?

1-888-768-2913